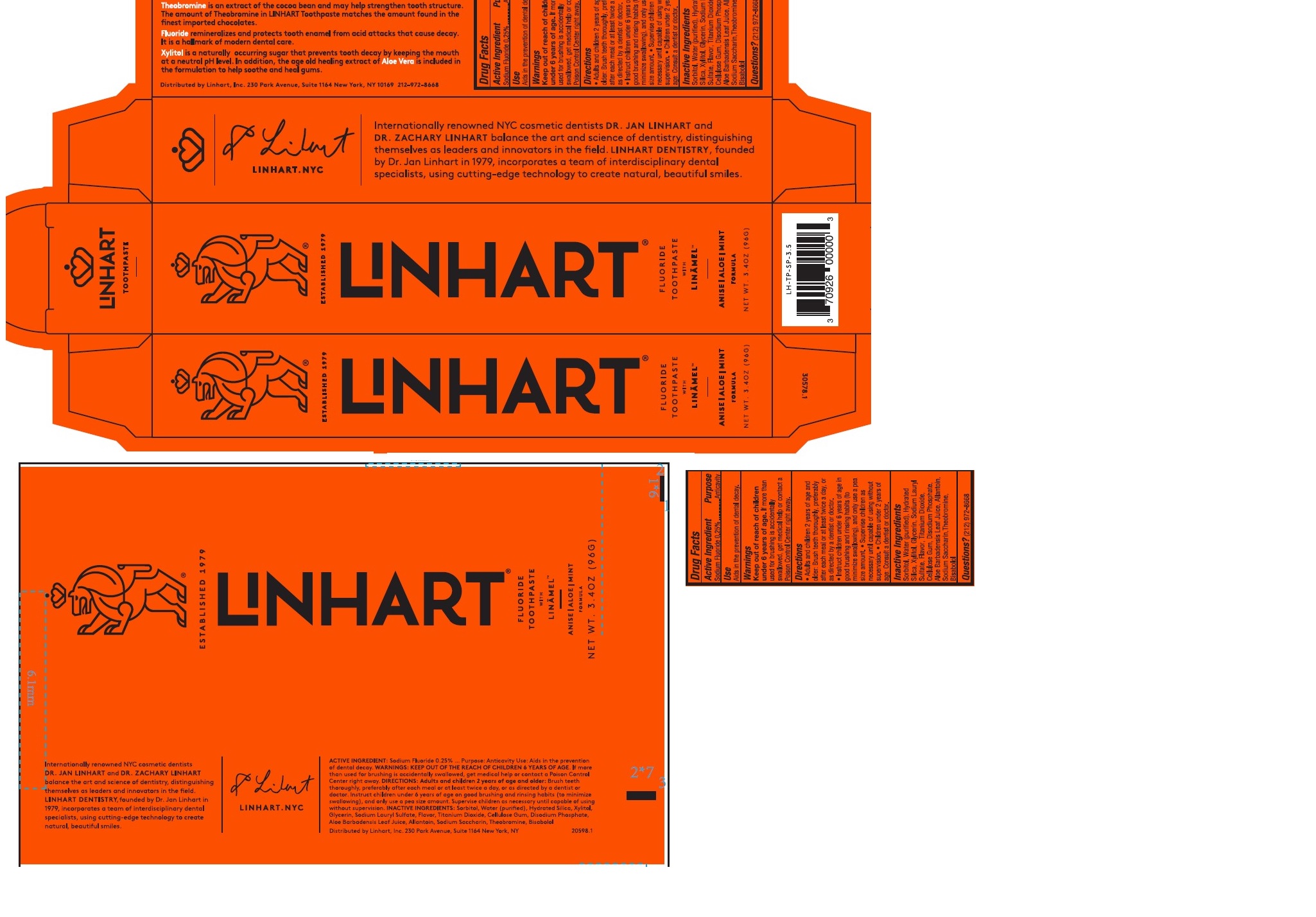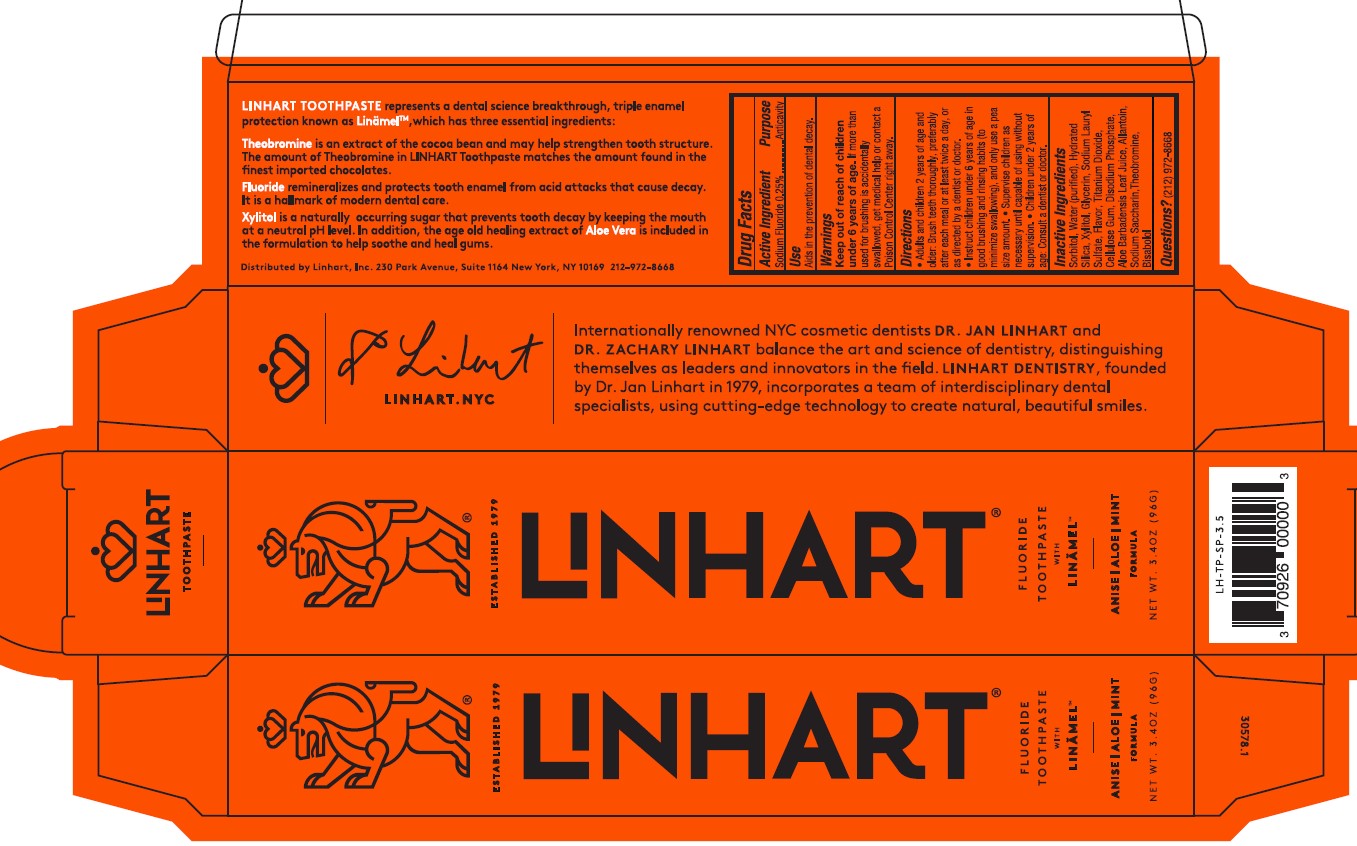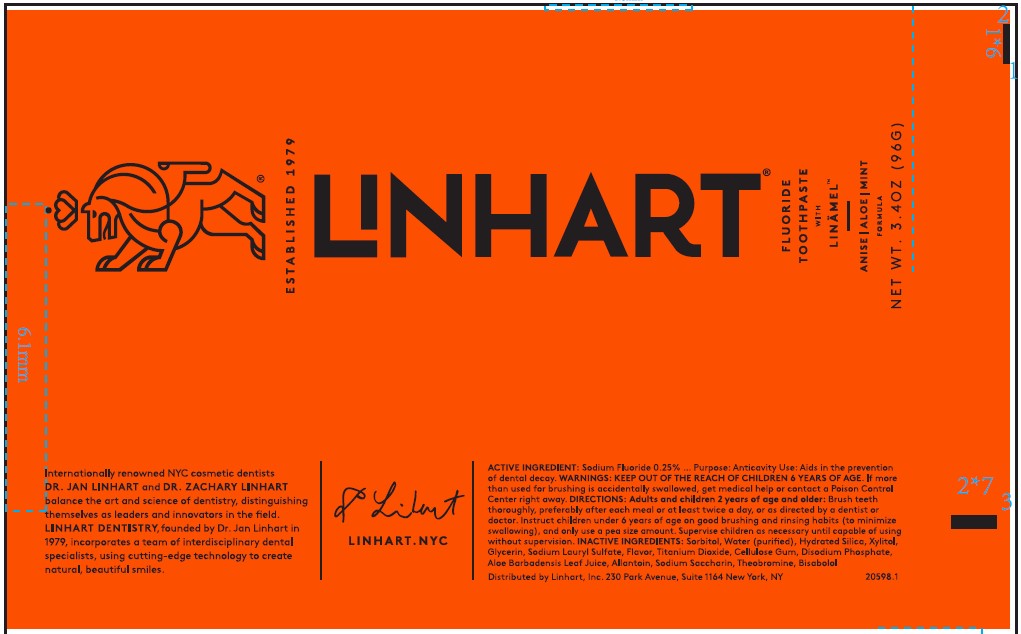 DRUG LABEL: LINHART
NDC: 73333-096 | Form: PASTE, DENTIFRICE
Manufacturer: Nutrix International,LLC
Category: otc | Type: HUMAN OTC DRUG LABEL
Date: 20200116

ACTIVE INGREDIENTS: SODIUM FLUORIDE 2.5 mg/1 g
INACTIVE INGREDIENTS: SORBITOL; HYDRATED SILICA; SODIUM LAURYL SULFATE; SODIUM PHOSPHATE, DIBASIC, DIHYDRATE; WATER; GLYCERIN; SILICON DIOXIDE; TITANIUM DIOXIDE; CARBOXYMETHYLCELLULOSE; ALOE VERA LEAF; SACCHARIN SODIUM; .ALPHA.-BISABOLOL, (+/-)-; THEOBROMINE; XYLITOL; ALLANTOIN

Active Ingredient

Sodium Fluoride 0.25%

Purpose

Anticavity

Indications and Usage

Aids in the prevention of dental decay.

Warnings

If more than used for brushing is accidentally swallowed, get medical help or contact a Poison Control Center right away.

Keep out of reach section

Keep out of reach of children under 6 years of age.

Directions

- Adults and Children 2 years of age and older: Brush teeth thoroughly, preferably after each meal or at least twice a day, or as directed by a dentist or doctor.
- Instruct children 6 years of age in good brushing and rinsing habits (to minimize swallowing), and and only use a pea size amount.
- Supervise children as necessary until capable of using without supervision.
- Children under 2 years of age: Consult a dentist or doctor.

Inactive Ingredients

Sorbitol, Water (Purified), Hydrated Silica, Xylitol, Glycerin, Sodium Lauryl Sulfate, Flavor, Titanium Dioxide, Cellulose Gum,Disodium Phosphate, Aloe Barbadensis Leaf Juice, Allantoin, Sodium Saccharin, Theobromine,Bisobolol.

Questions

(212) 599-2397